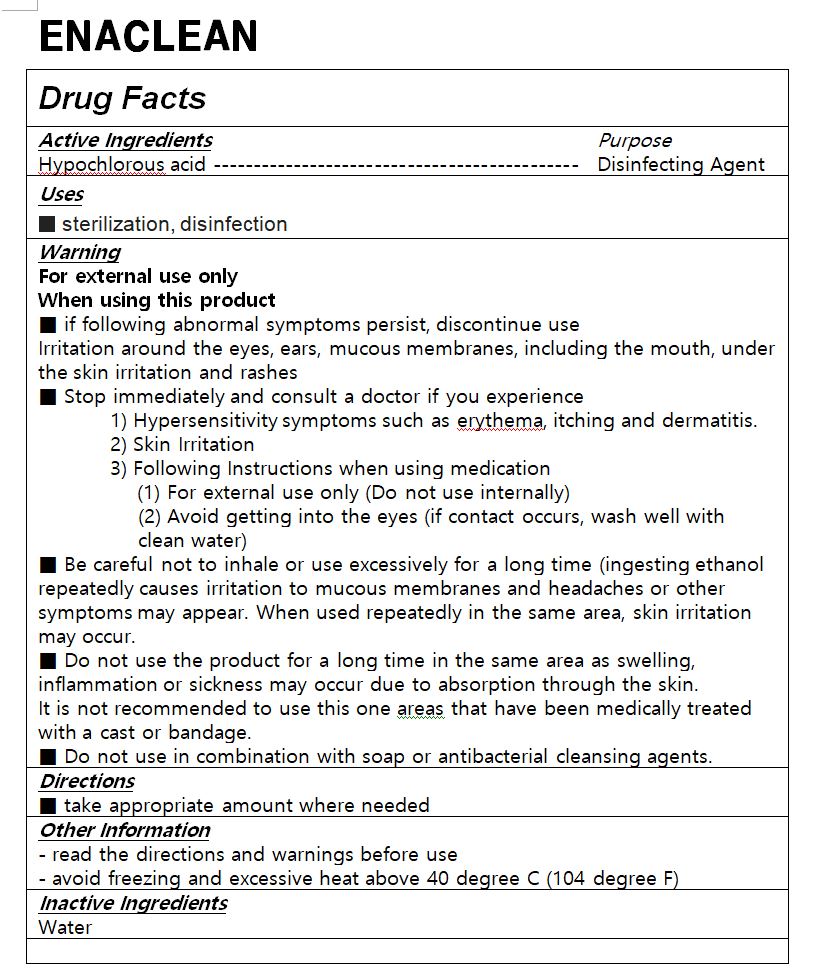 DRUG LABEL: ENACLEAN
NDC: 75696-0007 | Form: LIQUID
Manufacturer: JD corporation
Category: otc | Type: HUMAN OTC DRUG LABEL
Date: 20210201

ACTIVE INGREDIENTS: HYPOCHLOROUS ACID 0.005 g/100 mL
INACTIVE INGREDIENTS: WATER

Drug Facts

ACTIVE INGREDIENT

hypochlorous acid

PURPOSE

sterilization, disinfection

KEEP OUT OF REACH OF THE CHILDREN

INDICATIONS AND USAGE

take appropriate amount where needed

WARNINGS

■ Flammable. Keep away from fire or flame.

■ For external use only.

■ Do not use in eyes.

■ lf swallowed, get medical help promptly.

■ Stop use, ask doctor lf irritation occurs.

■ Keep out of reach of children.

DOSAGE AND ADMINISTRATION

for external use only

INACTIVE INGREDIENT

water